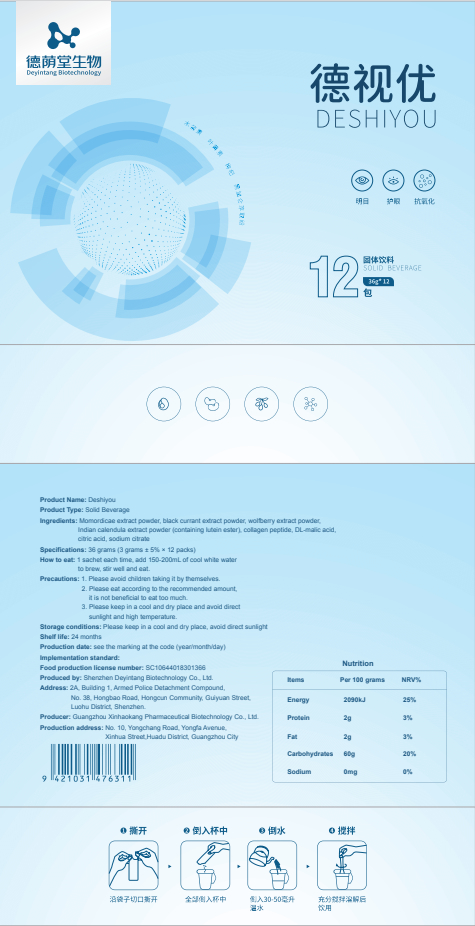 DRUG LABEL: Deshiyou
NDC: 82570-003 | Form: POWDER
Manufacturer: Shenzhen Deyintang Biotechnology Co., Ltd.
Category: otc | Type: HUMAN OTC DRUG LABEL
Date: 20220221

ACTIVE INGREDIENTS: COLLAGEN, SOLUBLE, FISH SKIN 33 g/100 g; MOMORDICA CHARANTIA FRUIT 2 g/100 g; LYCIUM BARBARUM FRUIT 7 g/100 g; CALENDULA OFFICINALIS FLOWERING TOP 7 g/100 g; SALVIA MICROPHYLLA WHOLE 2 g/100 g
INACTIVE INGREDIENTS: MALIC ACID; CITRIC ACID MONOHYDRATE; SODIUM CITRATE

ACTIVE INGREDIENT

Momordicae extract powder, black currant extract powder, wolfberry extract powder,Indian calendula extract powder (containing lutein ester), collagen peptide

INACTIVE INGREDIENT

DL-malic acid,citric acid, sodium citrate

PURPOSE

health care

Please avoid children taking it by themselves.

How to eat

1 sachet each time, add 150-200mL of cool white water to brew, stir well and eat.

INDICATIONS AND USAGE

Please eat according to the recommended amount,it is not beneficial to eat too much.

Storage conditions

Please keep in a cool and dry place, avoid direct sunlight

WARNINGS

1.Please avoid children taking it by themselves.
2. Please eat according to the recommended amount,it is not beneficial to eat too much.
3. Please keep in a cool and dry place and avoid directsunlight and high temperature.